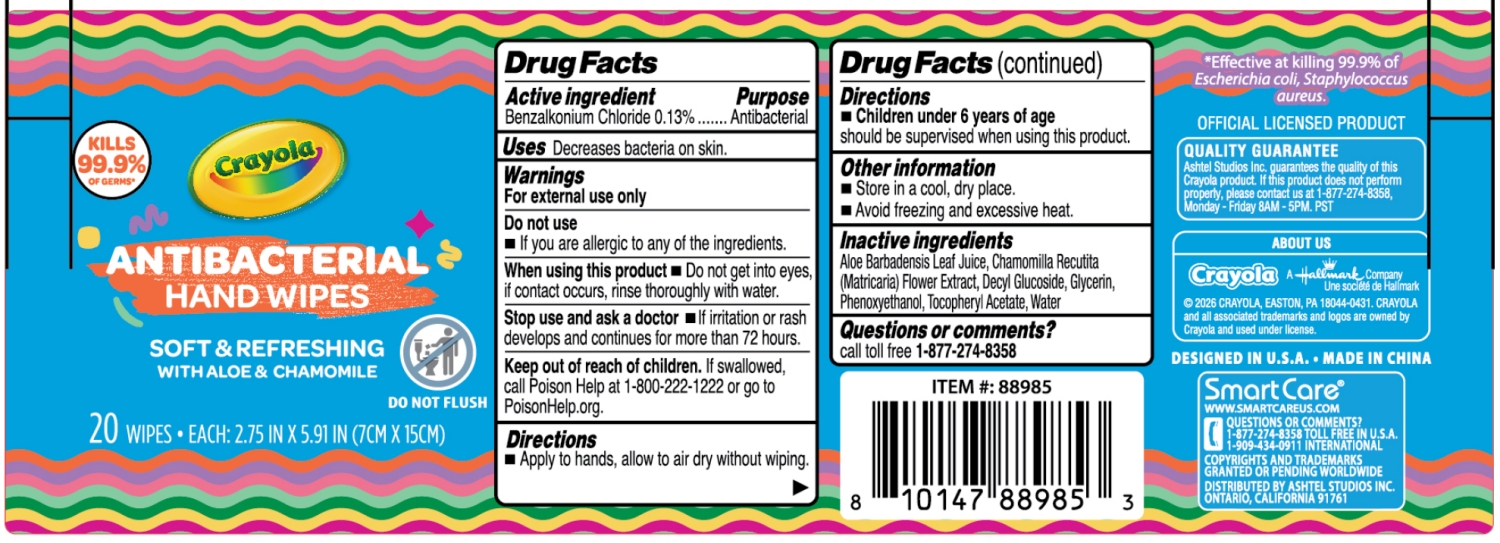 DRUG LABEL: Crayola ANTIBACTERIAL HAND WIPES
NDC: 70108-310 | Form: CLOTH
Manufacturer: ASHTEL STUDIOS INC.
Category: otc | Type: HUMAN OTC DRUG LABEL
Date: 20260210

ACTIVE INGREDIENTS: BENZALKONIUM CHLORIDE 0.13 g/100 g
INACTIVE INGREDIENTS: DECYL GLUCOSIDE; ALOE BARBADENSIS LEAF JUICE; GLYCERIN; .ALPHA.-TOCOPHEROL ACETATE; WATER; PHENOXYETHANOL; CHAMOMILE

70108-310 Crayola ANTIBACTERIAL HAND WIPES

Active ingredient

Benzalkonium Chloride 0.13%

Purpose

Antibacterial

INDICATIONS AND USAGE

Uses Decreases bacteria on skin.

Warnings

For external use only.

Do not use

■ If you are allergic to any of the ingredients.

When using this product ■ Do not get into eyes, if contact occurs, rinse thoroughly with water.

Stop use and ask a doctor ■ If irritation or rash develops and continues for more than 72 hours.

Keep out of reach of children. If swallowed, call Poison Help at 1-800-222-1222 or go to PoisonHelp.org.

Directions

■ Apply to hands, allow to air dry without wiping.

■ Children under 6 years of age

should be supervised when using this product.

Other information

■ Store in a cool, dry place.

■ Avoid freezing and excessive heat.

Inactive ingredients

Aloe Barbadensis Leaf Juice, Chamomilla Recutita (Matricaria) Flower Extract, Decyl Glucoside, Glycerin, Phenoxyethanol, TocopheryI Acetate, Water

PACKAGE LABEL

20 WIPES·EACH: 2.75 IN × 5.91 IN (7CM × 15CM)

NDC: 70108-310-01